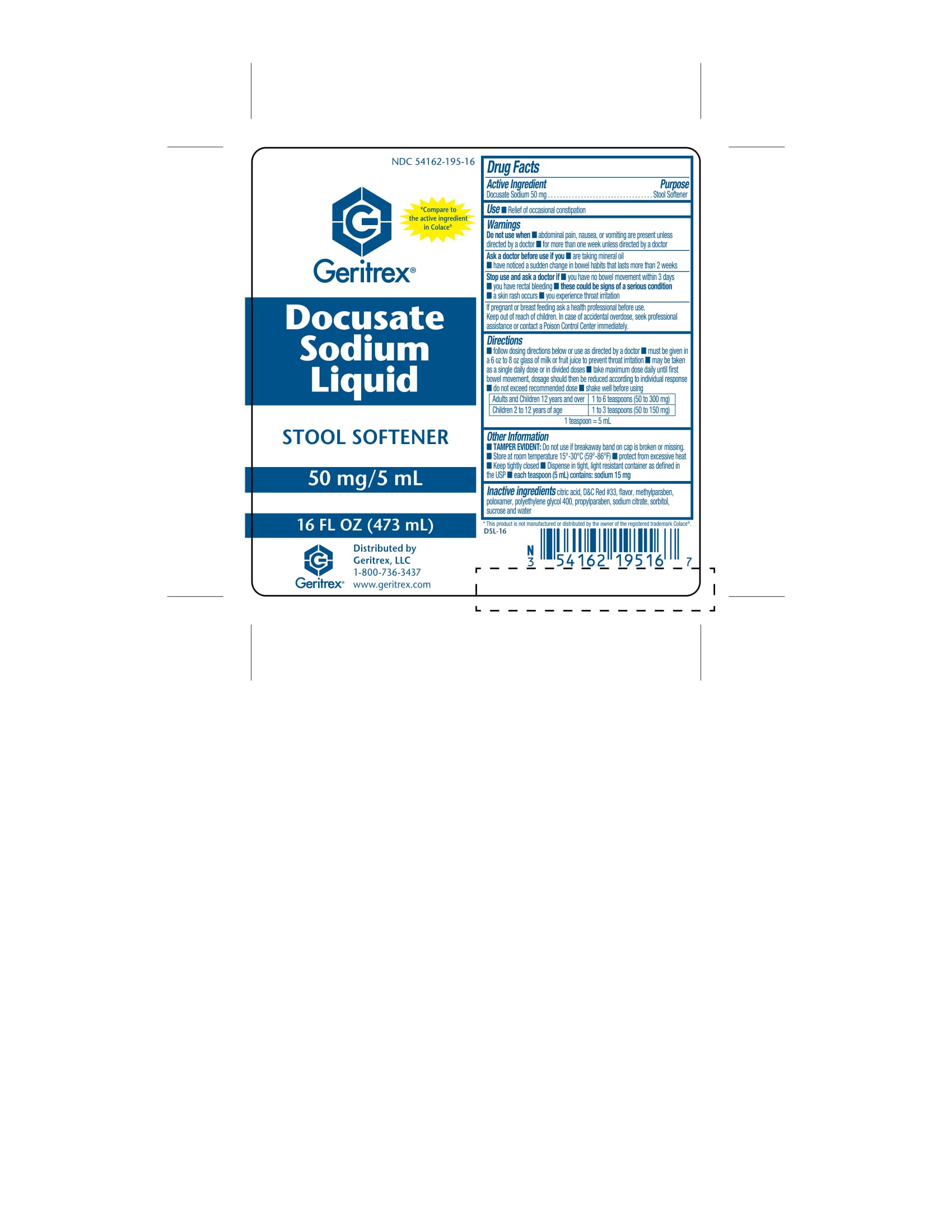 DRUG LABEL: Docusate Sodium Liquid
NDC: 54162-195 | Form: LIQUID
Manufacturer: Geritrex LLC
Category: otc | Type: HUMAN OTC DRUG LABEL
Date: 20170928

ACTIVE INGREDIENTS: Docusate sodium 50 mg/5 mL
INACTIVE INGREDIENTS: anhydrous citric acid; D&C red no. 33; methylparaben; propylparaben; POLYETHYLENE GLYCOL 400; sodium citrate; water; Poloxamer 407; SUCROSE; SORBITOL

Docusate Sodium Liquid

Active Ingredient (per teaspoonful = 5 mL)

Docusate Sodium 50 mg

Purpose

Stool Softener

Uses

- prevents / relieves dry hard stool
- results usually occur 1 to 3 days after the first dose

Warnings

Do not use

- when abdominal pain, nausea, or vomiting are present
- for more than one week unless directed by a doctor

Ask a doctor before use if you

- are taking mineral oil
- have noticed a sudden change in bowel habits that lasts more than 2 weeks

Stop use and ask a doctor if

- you have no bowel movement within 3 days
- you have rectal bleeding
- these could be signs of a serious condition
- a skin rash occurs
- you experience throat irritation

PREGNANCY OR BREAST FEEDING

If pregnant or breast feeding, ask a health professional before use.

Keep out of reach of children. In case of accidental overdose, seek professional assisstance or contact a Poison Control Center immediately.

Directions

- follow dosing directions below or take as directed by doctor
- must be given in a 6 to 8 oz glass of milk or fruit juice to prevent throat irritation
- may be taken as a single daily dose or in divided doses
- take maximum dose daily until first bowel movement, dosage should then be reduced according to individual response
- do not exceed recommended dose
- shake well before using

Adults and children 12 years and over | 1 to 6 teaspoons (50 to 300 mg)
Children 2 to 12 years of age | 1 to 3 teaspoons (50 to 150 mg)

1 teaspoon = 5 mL

TAMPER EVIDENT: Do not use if breakaway band on cap is broken or missing.

Other information

- Store at room temperature 15°-30°C (59°-86°F)
- protect from excessive heat
- Keep tightly closed
- Dispense in tight, light resistant container as defined in the USP
- each teaspoon (5 mL) contains: sodium 15 mg

Inactive ingredients

citric acid, D&C Red #33, flavor, methylparaben, parabens, poloxamer, polyethylene glycol 400, propylparaben, sodium citrate, sorbitol, sucrose, and water.